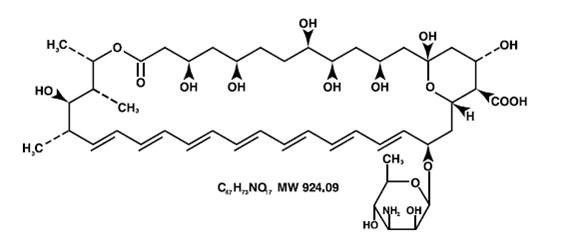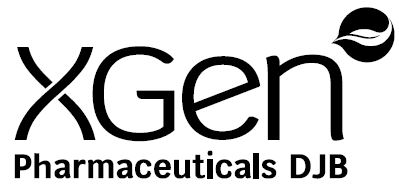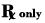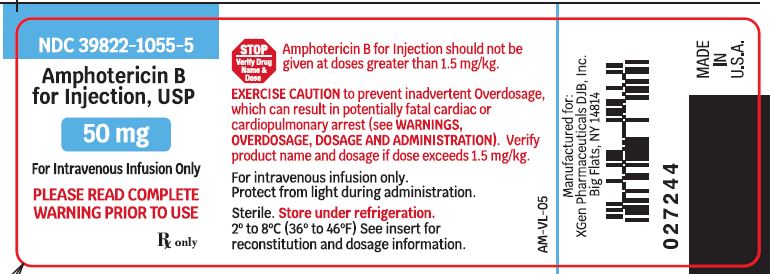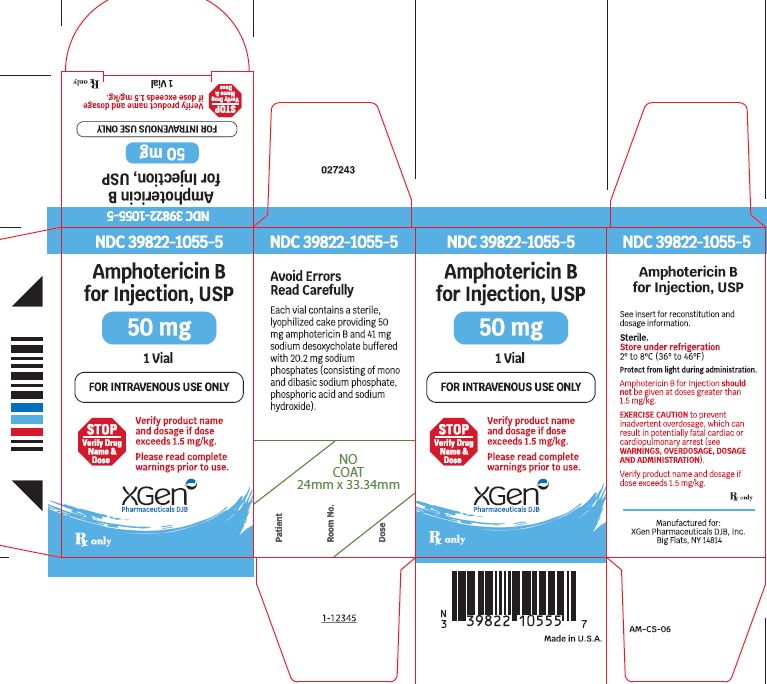 DRUG LABEL: Amphotericin B
NDC: 39822-1055 | Form: INJECTION, POWDER, LYOPHILIZED, FOR SOLUTION
Manufacturer: XGen Pharmaceuticals DJB, Inc.
Category: prescription | Type: HUMAN PRESCRIPTION DRUG LABEL
Date: 20220103

ACTIVE INGREDIENTS: AMPHOTERICIN B 50 mg/10 mL
INACTIVE INGREDIENTS: DEOXYCHOLIC ACID 38.75 mg/10 mL; SODIUM PHOSPHATE, DIBASIC 18.85 mg/10 mL; SODIUM PHOSPHATE, MONOBASIC, MONOHYDRATE 1.02 mg/10 mL; PHOSPHORIC ACID; SODIUM HYDROXIDE; NITROGEN

Amphotericin B for Injection USP
Rx Only

WARNING

This drug should be used primarily for treatment of patients with progressive and potentially life-threatening fungal infections; it should not be used to treat noninvasive forms of fungal disease such as oral thrush, vaginal candidiasis and esophageal candidiasis in patients with normal neutrophil counts.

Amphotericin B for Injection should not be given in doses greater than 1.5 mg/kg.

EXERCISE CAUTION to prevent inadvertent overdosage, which may result in potentially fatal cardiac or cardiopulmonary arrest (see WARNINGS, OVERDOSAGE and DOSAGE AND ADMINISTRATION). Verify the product name and dosage pre-administration, especially if dose exceeds 1.5 mg/kg.

DESCRIPTION

Amphotericin B for Injection USP contains amphotericin B, an antifungal polyene antibiotic obtained from a strain of Streptomyces nodosus. Amphotericin B is designated chemically as [1R- (1R*, 3S*, 5R*, 6R*, 9R*, 11R*, 15S*, 16R*, 17R*, 18S*, 19E, 21E, 23E, 25E, 27E, 29E, 31E, 33R*, 35S*, 36R*, 37S*)] -33-[(3-Amino-3, 6-dideoxy-β-D-mannopyranosyl)-oxy]-1,3,5,6,9,11,17,37-octahydroxy-15,16,18-trimethyl-13-oxo-14,39-dioxabicyclo [33.3.1] nonatriaconta-19,21,23,25,27,29,31-heptaene-36-carboxylic acid. Structural formula:

Each vial contains a sterile, nonpyrogenic, lyophilized cake (which may partially reduce to powder following manufacture) providing 50 mg amphotericin B and 41 mg sodium desoxycholate buffered with 20.2 mg sodium phosphates (consisting of mono and dibasic sodium phosphate, phosphoric acid and sodium hydroxide). Crystalline amphotericin B is insoluble in water; therefore, the antibiotic is solubilized by the addition of sodium desoxycholate to form a mixture which provides a colloidal dispersion for intravenous infusion following reconstitution.

At the time of manufacture the air in the vial is replaced by nitrogen.

CLINICAL PHARMACOLOGY

Microbiology

Amphotericin B shows a high order of in vitro activity against many species of fungi. Histoplasma capsulatum, Coccidioides immitis, Candida species, Blastomyces dermatitidis, Rhodotorula, Cryptococcus neoformans, Sporothrix schenckii, Mucor mucedo, and Aspergillus fumigatus are all inhibited by concentrations of amphotericin B ranging from 0.03 to 1.0 mcg/mL in vitro. While Candida albicans is generally quite susceptible to amphotericin B, non-albicans species may be less susceptible. Pseudallescheria boydii and Fusarium sp. are often resistant to amphotericin B. The antibiotic is without effect on bacteria, rickettsiae, and viruses.

Susceptibility Testing

Standardized techniques for susceptibility testing for antifungal agents have not been established and results of susceptibility studies have not been correlated with clinical outcomes.

Pharmacokinetics

Amphotericin B is fungistatic or fungicidal depending on the concentration obtained in body fluids and the susceptibility of the fungus. The drug acts by binding to sterols in the cell membrane of susceptible fungi with a resultant change in membrane permeability allowing leakage of intracellular components. Mammalian cell membranes also contain sterols and it has been suggested that the damage to human cells and fungal cells may share common mechanisms.

An initial intravenous infusion of 1 to 5 mg of amphotericin B per day, gradually increased to 0.4 to 0.6 mg/kg daily, produces peak plasma concentrations ranging from approximately 0.5 to 2 mcg/mL. Following a rapid initial fall, plasma concentrations plateau at about 0.5 mcg/mL. An elimination half-life of approximately 15 days follows an initial plasma half-life of about 24 hours. Amphotericin B circulating in plasma is highly bound (>90%) to plasma proteins and is poorly dialyzable. Approximately two thirds of concurrent plasma concentrations have been detected in fluids from inflamed pleura, peritoneum, synovium, and aqueous humor. Concentrations in the cerebrospinal fluid seldom exceed 2.5% of those in the plasma. Little amphotericin B penetrates into vitreous humor or normal amniotic fluid. Complete details of tissue distribution are not known.

Amphotericin B is excreted very slowly (over weeks to months) by the kidneys with 2 to 5% of a given dose being excreted in the biologically active form. Details of possible metabolic pathways are not known. After treatment is discontinued, the drug can be detected in the urine for at least 7 weeks due to the slow disappearance of the drug. The cumulative urinary output over a 7 day period amounts to approximately 40% of the amount of drug infused.

INDICATIONS & USAGE

Amphotericin B for Injection USP should be administered primarily to patients with progressive, potentially life-threatening fungal infections. This potent drug should not be used to treat noninvasive fungal infections, such as oral thrush, vaginal candidiasis and esophageal candidiasis in patients with normal neutrophil counts.

Amphotericin B for Injection USP is specifically intended to treat potentially life-threatening fungal infections: aspergillosis, cryptococcosis (torulosis), North American blastomycosis, systemic candidiasis, coccidioido-mycosis, histoplasmosis, zygomycosis including mucormycosis due to susceptible species of the genera Absidia, Mucor and Rhizopus, and infections due to related susceptible species of Conidiobolus and Basidiobolus, and sporotrichosis.

Amphotericin B may be useful in the treatment of American mucocutaneous leishmaniasis, but it is not the drug of choice as primary therapy.

CONTRAINDICATIONS

This product is contraindicated in those patients who have shown hypersensitivity to amphotericin B or any other component in the formulation unless, in the opinion of the physician, the condition requiring treatment is life-threatening and amenable only to amphotericin B therapy.

WARNINGS

Amphotericin B is frequently the only effective treatment available for potentially life-threatening fungal disease. In each case, its possible life-saving benefit must be balanced against its untoward and dangerous side effects.

EXERCISE CAUTION to prevent inadvertent Amphotericin B for Injection overdose, which can result in potentially fatal cardiac or cardiopulmonary arrest. Verify the product name and dosage dosage pre-administration, especially if dose exceeds 1.5 mg/kg. (see OVERDOSAGE and DOSAGE AND ADMINISTRATION)

PRECAUTIONS

General

Amphotericin B should be administered intravenously under close clinical observation by medically trained personnel. It should be reserved for treatment of patients with progressive, potentially life-threatening fungal infections due to susceptible organisms (see INDICATIONS AND USAGE).

Acute reactions including fever, shaking chills, hypotension, anorexia, nausea, vomiting, headache, and tachypnea are common 1 to 3 hours after starting an intravenous infusion. These reactions are usually more severe with the first few doses of amphotericin B and usually diminish with subsequent doses.

Rapid intravenous infusion has been associated with hypotension, hypokalemia, arrhythmias, and shock and should, therefore, be avoided (see DOSAGE AND ADMINISTRATION).

Amphotericin B should be used with care in patients with reduced renal function; frequent monitoring of renal function is recommended (see PRECAUTIONS: Laboratory Tests and ADVERSE REACTIONS). In some patients hydration and sodium repletion prior to amphotericin B administration may reduce the risk of developing nephrotoxicity. Supplemental alkali medication may decrease renal tubular acidosis complications.

Since acute pulmonary reactions have been reported in patients given amphotericin B during or shortly after leukocyte transfusions, it is advisable to temporarily separate these infusions as far as possible and to monitor pulmonary function (see PRECAUTIONS: Drug Interactions).

Leukoencephalopathy has been reported following use of amphotericin B. Literature reports have suggested that total body irradiation may be a predisposition.

Whenever medication is interrupted for a period longer than 7 days, therapy should be resumed by starting with the lowest dosage level, e.g., 0.25 mg/kg of body weight, and increased gradually as outlined under DOSAGE AND ADMINISTRATION.

Laboratory Tests

Renal function should be monitored frequently during amphotericin B therapy (see ADVERSE REACTIONS). It is also advisable to monitor on a regular basis liver function, serum electrolytes (particularly magnesium and potassium), blood counts, and hemoglobin concentrations. Laboratory test results should be used as a guide to subsequent dosage adjustments.

Drug Interactions

When administered concurrently, the following drugs may interact with amphotericin B:

Antineoplastic agents: may enhance the potential for renal toxicity, bronchospasm and hypotension. Antineoplastic agents (e.g., nitrogen mustard, etc.) should be given concomitantly only with great caution.

Corticosteroids and Corticotropin (ACTH): may potentiate amphotericin B-induced hypokalemia which may predispose the patient to cardiac dysfunction. Avoid concomitant use unless necessary to control side effects of amphotericin B. If used concomitantly, closely monitor serum electrolytes and cardiac function (see ADVERSE REACTIONS).

Digitalis glycosides: amphotericin B-induced hypokalemia may potentiate digitalis toxicity. Serum potassium levels and cardiac function should be closely monitored and any deficit promptly corrected.

Flucytosine: while a synergistic relationship with amphotericin B has been reported, concomitant use may increase the toxicity of flucytosine by possibly increasing its cellular uptake and/or impairing its renal excretion.

Imidazoles (e.g., ketoconazole, miconazole, clotrimazole, fluconazole, etc.): in vitro and animal studies with the combination of amphotericin B and imidazoles suggest that imidazoles may induce fungal resistance to amphotericin B. Combination therapy should be administered with caution, especially in immunocompromised patients.

Other nephrotoxic medications: agents such as aminoglycosides, cyclosporine, and pentamidine may enhance the potential for drug-induced renal toxicity, and should be used concomitantly only with great caution. Intensive monitoring of renal function is recommended in patients requiring any combination of nephrotoxic medications (see PRECAUTIONS: Laboratory Tests).

Skeletal muscle relaxants: amphotericin B-induced hypokalemia may enhance the curariform effect of skeletal muscle relaxants (e.g., tubocurarine). Serum potassium levels should be monitored and deficiencies corrected.

Leukocyte transfusions: acute pulmonary toxicity has been reported in patients receiving intravenous amphotericin B and leukocyte transfusions (see PRECAUTIONS: General).

Carcinogenesis, Mutagenesis, Impairment of Fertility

No long-term studies in animals have been performed to evaluate carcinogenic potential. There also have been no studies to determine mutagenicity or whether this medication affects fertility in males or females.

Pregnancy

Teratogenic Effects

Pregnancy Category B: Reproduction studies in animals have revealed no evidence of harm to the fetus due to amphotericin B for injection. Systemic fungal infections have been successfully treated in pregnant women with amphotericin B for injection without obvious effects to the fetus, but the number of cases reported has been small. Because animal reproduction studies are not always predictive of human response, and adequate and well-controlled studies have not been conducted in pregnant women, this drug should be used during pregnancy only if clearly indicated.

Nursing Mothers

It is not known whether amphotericin B is excreted in human milk. Because many drugs are excreted in human milk and considering the potential toxicity of amphotericin B, it is prudent to advise a nursing mother to discontinue nursing.

Pediatric Use

Safety and effectiveness in pediatric patients have not been established through adequate and well-controlled studies. Systemic fungal infections have been successfully treated in pediatric patients without reports of unusual side effects. Amphotericin B for Injection when administered to pediatric patients should be limited to the smallest dose compatible with an effective therapeutic regimen.

ADVERSE REACTIONS

Although some patients may tolerate full intravenous doses of amphotericin B without difficulty, most will exhibit some intolerance, often at less than the full therapeutic dose.

Tolerance may be improved by treatment with aspirin, antipyretics (e.g., acetaminophen), antihistamines, or antiemetics. Meperidine (25 to 50 mg IV) has been shown in some patients to decrease the duration of shaking chills and fever that may accompany the infusion of amphotericin B.

Administration of amphotericin B on alternate days may decrease anorexia and phlebitis.

Intravenous administration of small doses of adrenal corticosteroids just prior to or during the amphotericin B infusion may help decrease febrile reactions. Dosage and duration of such corticosteroid therapy should be kept to a minimum (see PRECAUTIONS: Drug Interactions).

Addition of heparin (1000 units per infusion), and the use of a pediatric scalp-vein needle may lessen the incidence of thrombophlebitis. Extravasation may cause chemical irritation.

The adverse reactions most commonly observed are:

General (body as a whole): fever (sometimes accompanied by shaking chills usually occurring within 15 to 20 minutes after initiation of treatment); malaise; weight loss.

Cardiopulmonary: hypotension; tachypnea.

Gastrointestinal: anorexia; nausea; vomiting; diarrhea; dyspepsia; cramping epigastric pain.

Hematologic: normochromic, normocytic anemia.

Local: pain at the injection site with or without phlebitis or thrombophlebitis.

Musculoskeletal: generalized pain, including muscle and joint pains.

Neurologic: headache.

Renal: decreased renal function and renal function abnormalities including: azotemia, hypokalemia, hyposthenuria, renal tubular acidosis; and nephrocalcinosis. These usually improve with interruption of therapy. However, some permanent impairment often occurs, especially in those patients receiving large amounts (over 5 g) of amphotericin B or receiving other nephrotoxic agents. In some patients hydration and sodium repletion prior to amphotericin B administration may reduce the risk of developing nephrotoxicity. Supplemental alkali medication may decrease renal tubular acidosis.

The following adverse reactions have also been reported:

General (body as a whole): flushing.

Allergic: anaphylactoid and other allergic reactions; bronchospasm; wheezing.

Cardiopulmonary: cardiac arrest; shock; cardiac failure; pulmonary edema; hypersensitivity pneumonitis; arrhythmias, including ventricular fibrillation; dyspnea; hypertension.

Dermatologic: rash, in particular maculopapular; pruritus. Skin exfoliation, toxic epidermal necrolysis, and Stevens-Johnson syndrome have been reported during post-marketing surveillance.

Gastrointestinal: acute liver failure; hepatitis; jaundice; hemorrhagic gastroenteritis; melena.

Hematologic: agranulocytosis; coagulation defects; thrombocytopenia; leukopenia; eosinophilia; leukocytosis.

Neurologic: convulsions; hearing loss; tinnitus; transient vertigo; visual impairment; diplopia; peripheral neuropathy; encephalopathy (see PRECAUTIONS); other neurologic symptoms.

Renal: acute renal failure; anuria; oliguria. Nephrogenic diabetes insipidus has been reported during post-marketing surveillance.

Altered Laboratory Findings
Serum Electrolytes: Hypomagnesemia; hypo- and hyperkalemia; hypocalcemia.

Liver Function Tests: Elevations of AST, ALT, GGT, bilirubin, and alkaline phosphatase.

Renal Function Tests: Elevations of BUN and serum creatinine.

OVERDOSAGE

Amphotericin B overdoses can result in potentially fatal cardiac or cardiopulmonary arrest (see WARNINGS and DOSAGE AND ADMINISTRATION). If an overdose is suspected, discontinue therapy and monitor the patient's clinical status (e.g., cardiorespiratory, renal, and liver function, hematologic status, serum electrolytes) and administer supportive therapy, as required. Amphotericin B is not hemodialyzable.

Prior to reinstituting therapy, the patient's condition should be stabilized (including correction of electrolyte deficiencies, etc.).

DOSAGE & ADMINISTRATION

**VERIFY PRODUCT NAME AND DOSAGE.**

CAUTION: Under no circumstances should a total daily dose of 1.5 mg/kg be exceeded.

Amphotericin B overdoses can result in potentially fatal cardiac or cardiopulmonary arrest (see WARNINGS and OVERDOSAGE).

Amphotericin B for Injection should be administered by slow intravenous infusion. Intravenous infusion should be given over a period of approximately 2 to 6 hours (depending on the dose) observing the usual precautions for intravenous therapy (see PRECAUTIONS: General). The recommended concentration for intravenous infusion is 0.1 mg/mL (1mg/10mL).

Since patient tolerance varies greatly, the dosage of amphotericin B must be individualized and adjusted according to the patient's clinical status (e.g., site and severity of infection, etiologic agent, cardio-renal function, etc.).

A single intravenous test dose (1 mg in 20 mL of 5% dextrose solution) administered over 20 to 30 minutes may be preferred. The patient's temperature, pulse, respiration, and blood pressure should be recorded every 30 minutes for 2 to 4 hours.

In patients with good cardio-renal function and a well tolerated test dose, therapy is usually initiated with a daily dose of 0.25 mg/kg of body weight. However, in those patients having severe and rapidly progressive fungal infection, therapy may be initiated with a daily dose of 0.3 mg/kg of body weight. In patients with impaired cardio-renal function or a severe reaction to the test dose, therapy should be initiated with smaller daily doses (i.e., 5 to 10 mg).

Depending on the patient's cardio-renal status (see PRECAUTIONS: Laboratory Tests), doses may gradually be increased by 5 to 10 mg per day to final daily dosage of 0.5 to 0.7 mg/kg.

There are insufficient data presently available to define total dosage requirements and duration of treatment necessary for eradication of specific mycoses. The optimal dose is unknown. Total daily dosage may range up to 1.0 mg/kg per day or up to 1.5 mg/kg when given on alternate days.

Sporotrichosis: Therapy with intravenous amphotericin B for sporotrichosis has ranged up to nine months with a total dose up to 2.5 g.

Aspergillosis: Aspergillosis has been treated with amphotericin B intravenously for a period up to 11 months with a total dose up to 3.6 g.

Rhinocerebral phycomycosis: This fulminating disease generally occurs in association with diabetic ketoacidosis. It is, therefore, imperative that diabetic control be restored in order for treatment with Amphotericin B for Injection to be successful. In contradistinction, pulmonary phycomycosis, which is more common in association with hematologic malignancies, is often an incidental finding at autopsy. A cumulative dose of at least 3 g of amphotericin B is recommended to treat rhinocerebral phycomycosis. Although a total dose of 3 to 4 g will infrequently cause lasting renal impairment, this would seem a reasonable minimum where there is clinical evidence of invasion of deep tissue. Since rhinocerebral phycomycosis usually follows a rapidly fatal course, the therapeutic approach must necessarily be more aggressive than that used in more indolent mycoses.

Preparation of Solutions
Reconstitute as follows: An initial concentrate of 5 mg amphotericin B per mL is first prepared by rapidly expressing 10 mL Sterile Water for Injection USP without a bacteriostatic agent directly into the lyophilized cake, using a sterile needle (minimum diameter: 20 gauge) and syringe. Shake the vial immediately until the colloidal solution is clear. The infusion solution, providing 0.1 mg amphotericin B per mL, is then obtained by further dilution (1:50) with 5% Dextrose Injection USP of pH above 4.2. The pH of each container of Dextrose Injection should be ascertained before use. Commercial Dextrose Injection usually has a pH above 4.2; however, if it is below 4.2, then 1 or 2 mL of buffer should be added to the Dextrose Injection before it is used to dilute the concentrated solution of amphotericin B. The recommended buffer has the following composition:

Dibasic sodium phosphate (anhydrous) | 1.59 g
Monobasic sodium phosphate (anhydrous) | 0.96 g
Water for Injection USP | qs 100.0 mL

The buffer should be sterilized before it is added to the Dextrose Injection, either by filtration through a bacterial retentive stone, mat, or membrane, or by autoclaving for 30 minutes at 15 lb pressure (121˚C).

CAUTION: Aseptic technique must be strictly observed in all handling, since no preservative or bacteriostatic agent is present in the antibiotic or in the materials used to prepare it for administration. All entries into the vial or into the diluents must be made with a sterile needle. Do not reconstitute with saline solutions. The use of any diluent other than the ones recommended or the presence of a bacteriostatic agent (e.g., benzyl alcohol) in the diluent may cause precipitation of the antibiotic. Do not use the initial concentrate or the infusion solution if there is any evidence of precipitation or foreign matter in either one.

An in-line membrane filter may be used for intravenous infusion of amphotericin B; however, the mean pore diameter of the filter should not be less than 1.0 micron in order to assure passage of the antibiotic dispersion.

HOW SUPPLIED

Amphotericin B for Injection USP

Available as single vials providing 50 mg amphotericin B as a yellow to orange lyophilized cake (which may partially reduce to powder following manufacture). NDC 39822-1055-5. Retain in carton until time of use.

Storage

Prior to reconstitution Amphotericin B for Injection USP should be stored under refrigeration, 2˚ to 8˚C (36˚to 46˚F), protected against exposure to light. The concentrate (5 mg amphotericin B per mL after reconstitution with 10 mL Sterile Water for Injection USP) may be stored in the dark, at room temperature for 24 hours, or at refrigerator temperatures for one week with minimal loss of potency and clarity. Any unused material should then be discarded. Solutions prepared for intravenous infusion (0.1 mg or less amphotericin B per mL) should be used promptly after preparation and should be protected from light during administration.

Manufactured for:

XGen Pharmaceuticals DJB, Inc.
Big Flats, NY 14814

Revised October 2020
AM-PI-05
Printed in the USA

PRINCIPAL DISPLAY PANEL - Vial Label

NDC 39822-1055-5
Amphotericin B for Injection, USP
50mg
For Intravenous Infusion Only
Rx Only
1 Vial
XGen Pharmaceuticals DJB, Inc.
STOP: Verify product name & dosage if dose exceeds 1.5 mg/kg

PRINCIPAL DISPLAY PANEL - Carton

NDC 39822-1055-5
Amphotericin B for Injection, USP
50mg
For Intravenous Infusion Only
Rx Only
1 Vial
XGen Pharmaceuticals DJB, Inc.
STOP: Verify product name & dosage if dose exceeds 1.5 mg/kg